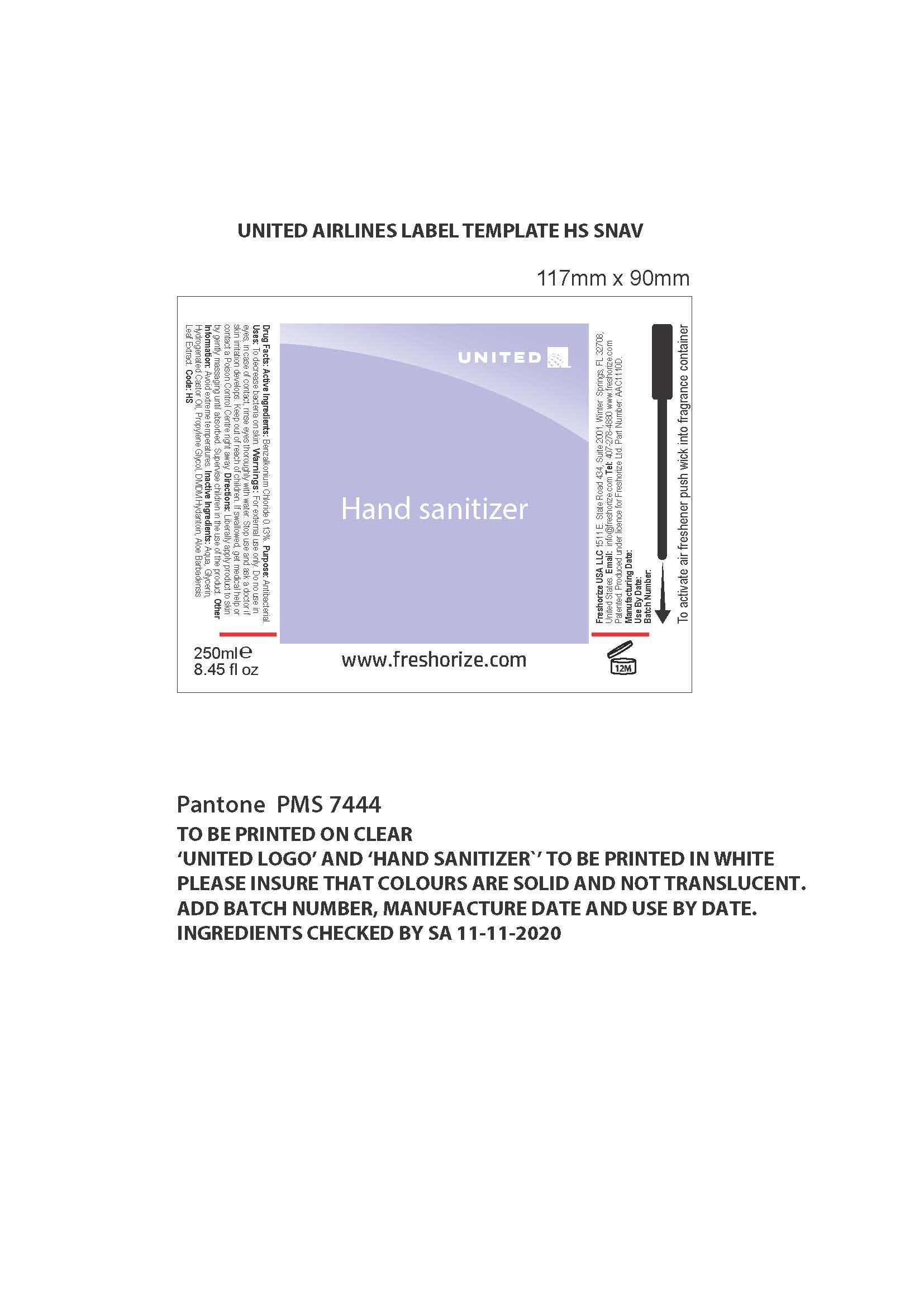 DRUG LABEL: United Airlines
NDC: 52305-601 | Form: LIQUID
Manufacturer: Freshorize Ltd
Category: otc | Type: HUMAN OTC DRUG LABEL
Date: 20251023

ACTIVE INGREDIENTS: BENZALKONIUM CHLORIDE 0.13 g/100 mL
INACTIVE INGREDIENTS: HYDROGENATED CASTOR OIL 0.75 g/100 mL; PROPYLENE 0.5 g/100 mL; WATER 95.07 g/100 mL; ALOE VERA LEAF 0.1 g/100 mL; GLYCERIN 3 g/100 mL; DMDM HYDANTOIN 0.2 g/100 mL

United Alcohol Free Hand Sanitizer

Uses:

To decrease bacteria on skin.

Warnings:

For external use only.
Do not use in eyes.
In cse of contact, rinse eyes thoroughly with water.
Stop use and ask a doctor is skin irritation develops.
If ingested, get medical help or contact a Poison Control Center immediately.

Warnings:

Keep out of reach of children.

Directions

Liberally apply product to skin by gently massaging until absorbed.
Supervise children in the use of this product.

Other Information:

Avoid extreme temperatures.

Inactive Ingredients:

Water (Aqua), Glycerin, Hydrogenated Castor Oil, DMDM Hydantoin, Propylene Glycol, Aloe Barbadensis Leaf Extract

Drug Facts:

Active Ingredients: Benzalkonium Chloride 0.13%

Purpose:

Antibacterial.

Product / Brand Name Label

Front Label

This product is a hand sanitizer liquid pump. There is no dosage. But typically a passenger will use 1-2 pumps.